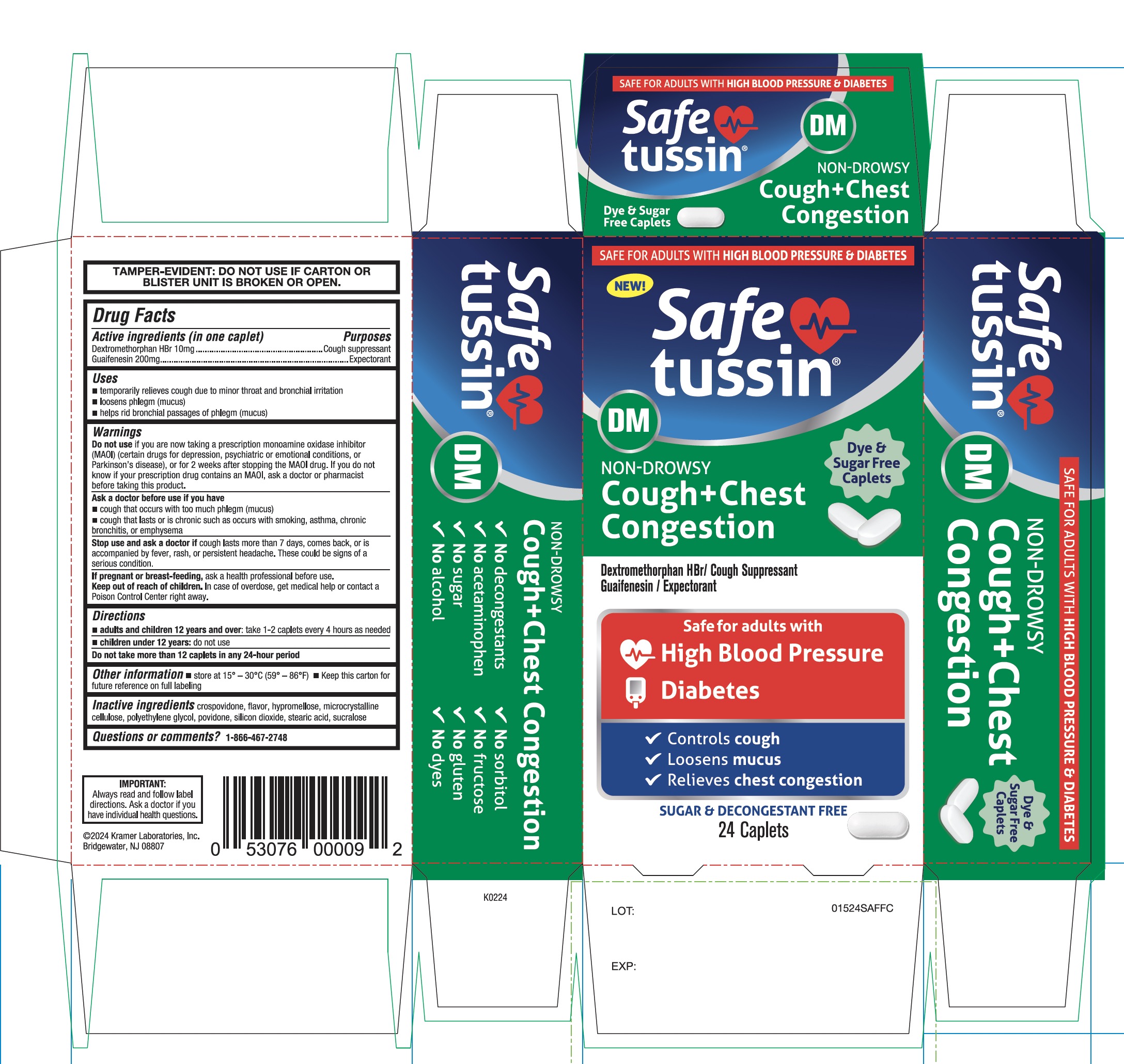 DRUG LABEL: SAFETUSSIN Non Drowsy
NDC: 55505-231 | Form: TABLET
Manufacturer: KRAMER LABORATORIES
Category: otc | Type: HUMAN OTC DRUG LABEL
Date: 20251223

ACTIVE INGREDIENTS: DEXTROMETHORPHAN HYDROBROMIDE 10 mg/1 1; GUAIFENESIN 200 mg/1 1
INACTIVE INGREDIENTS: CROSPOVIDONE (120 .MU.M); HYPROMELLOSE 2208 (100 MPA.S); MICROCRYSTALLINE CELLULOSE; POLYETHYLENE GLYCOL, UNSPECIFIED; POVIDONE, UNSPECIFIED; SILICON DIOXIDE; STEARIC ACID; SUCRALOSE

SAFETUSSIN Non-Drowsy Cough + Chest Congestion

Drug Facts

ACTIVE INGREDIENT

Active ingredients (in one caplet) | Purpose
Dextromethorphan HBr 10 mg | Cough suppressant
Guaifenesin 200 mg | Expectorant

Uses

- temporarily relieves cough due to minor throat and bronchial irritation
- loosen phlegm (mucus)
- helps rid bronchial passages of phlegm(mucus)

Warnings

Do not use

- if you are now taking a prescription monoamine oxidase inhibitor (MAOI) (certain drugs for depression, psychiatric or emotional conditions, or Parkinson's disease), or for 2 weeks after stopping the MAOI drug. If you do not know if your prescription drug contains an MAOI, ask a doctor or pharmacist before taking this product.

Ask a doctor before use if you have

- cough that occurs with too much phlegm (mucus)
- cough that lasts or is chronic such as occurs with smoking, asthma, chronic bronchitis or emphysema

Stop use and ask a doctor if

- cough lasts more than 7 days, comes back, or is accompanied by fever, rash, or persistent headache. These could be signs of a serious condition.

PREGNANCY OR BREAST FEEDING

If pregnant or breast-feeding, ask a health professional before use.

Keep out of reach of children.In case of overdose, get medical help or contact a Poison Control Center right away.

Directions

- adults and children 12 years and over: take 1-2 caplets every 4 hours as needed.
- Children under 12 years:do not use
  Do not take more than 12 caplets in any 24-hour period.

Other information

- Store at 15° - 30°C (59° - 86°F)
- Keep this carton for future reference on full labeling

Inactive ingredients

Crospovidone, flavor, Hypromellose, microcrystalline cellulose, polyethylene glycol, povidone, silicon dioxide, stearic acid, sucralose,

Questions or Comments?

1-866-467-2748

Distributed by

©2024 Kramer Laboratories, Inc Bridgewater, NJ 08807

PRINCIPAL DISPLAY PANEL - 236 ml Bottle Label

SAFE FOR ADULTS WITH HIGH BLOOD PRESSURE & DIABETES

NDC 55505-231-24

Safetussin® DM

NON-DROWSY

Cough+Chest

Congestion

Dextromethorphan HBr / Cough Suppressant

Guaifenesin / Expectorant

Safe for adults with

High Blood Pressure

Diabetes

- Control cough
- Loosens mucus
- Relives chest congestion

SUGAR & DECONGESTANT FREE
24 Caplets

- No decongestants
- No acetaminophen
- No Sugar
- No Alcohol
- No sorbitol
- No fructose
- No gluten
- No dyes